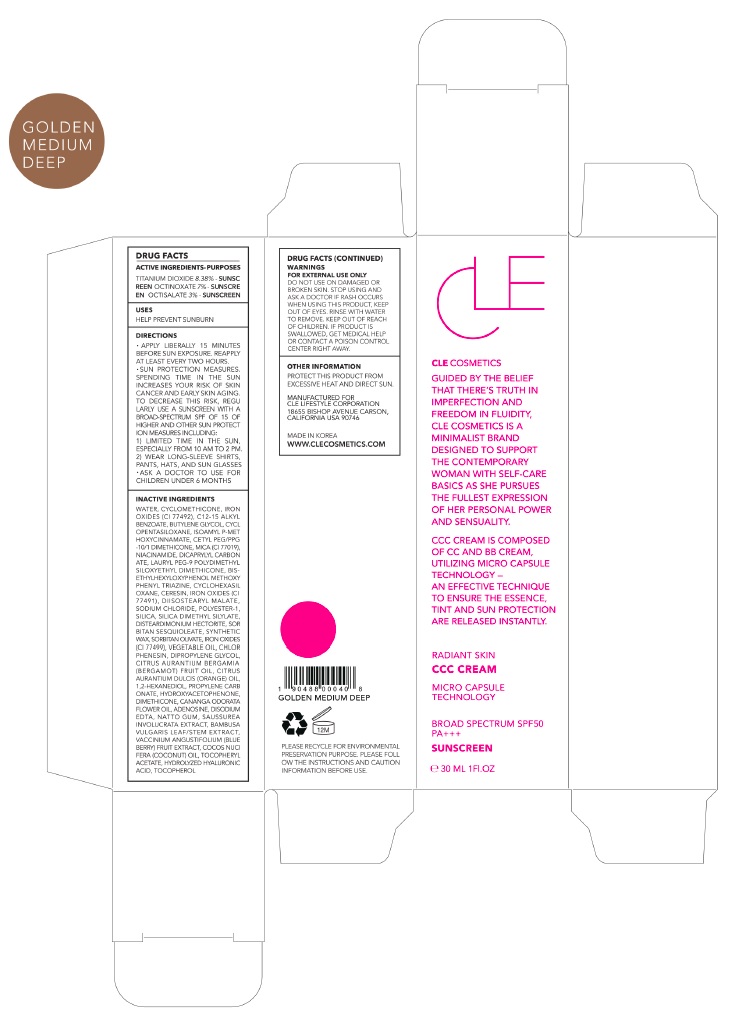 DRUG LABEL: CLE CCC Golden Medium Deep
NDC: 69231-027 | Form: CREAM
Manufacturer: KW ABSC, INC.
Category: otc | Type: HUMAN OTC DRUG LABEL
Date: 20181203

ACTIVE INGREDIENTS: OCTINOXATE 2.1 mg/30 mL; OCTISALATE 0.9 mg/30 mL; TITANIUM DIOXIDE 2.51454 mg/30 mL
INACTIVE INGREDIENTS: WATER; CYCLOMETHICONE; FERRIC OXIDE YELLOW; ALKYL (C12-15) BENZOATE; BUTYLENE GLYCOL; CYCLOMETHICONE 5; AMILOXATE; CETYL PEG/PPG-10/1 DIMETHICONE (HLB 2); MICA; NIACINAMIDE; DICAPRYLYL CARBONATE; LAURYL PEG-9 POLYDIMETHYLSILOXYETHYL DIMETHICONE; BEMOTRIZINOL; CERESIN; FERRIC OXIDE RED; DIISOSTEARYL MALATE; SODIUM CHLORIDE; SILICA DIMETHYL SILYLATE; DISTEARDIMONIUM HECTORITE; SORBITAN SESQUIOLEATE; SYNTHETIC WAX (1200 MW); SORBITAN OLIVATE; FERROSOFERRIC OXIDE; CORN OIL; CHLORPHENESIN; DIPROPYLENE GLYCOL; BERGAMOT OIL; ORANGE OIL; 1,2-HEXANEDIOL; PROPYLENE CARBONATE; HYDROXYACETOPHENONE; DIMETHICONE; CANANGA OIL; ADENOSINE; EDETATE DISODIUM ANHYDROUS

69231-027_CCC Golden Medium Deep

PURPOSE

Sunscreen

ACTIVE INGREDIENT

Titanium Dioxide 8.38%

Octinoxate 7%

Octisalate 3%

INDICATIONS AND USAGE

Helps prevent sunburn

DOSAGE AND ADMINISTRATION

Apply liberally 15 minutes before sun exposure. Reapply at least every two hours

Sun protection measures. Spending time in the sun increases your risk of skin cancer and early skin aging. To decrease this risk, regularly use a sunscreen with a broad spectrum SPF of 15 of higher and other sun protection measures including: 1) Limited time in the sun, especially from 10 am to 2 pm. 2) Wear long-sleeve shirts, pants, hats, and sunglasses
Ask a doctor to use for children under 6 months

WARNINGS

For external use only.
Do not use on damaged or broken skin.
When using this product, keep out of eyes. Rinse with water to remove.
Stop using and ask a doctor if rash occurs.

KEEP OUT OF REACH OF CHILDREN

Keep out of reach of the children. If product is swallowed, get medical help or contact a poison control center right away.

INACTIVE INGREDIENT

Water, Cyclomethicone, Iron Oxides (CI 77492), C12-15 Alkyl Benzoate, Butylene Glycol, Cyclopentasiloxane, Isoamyl p-Methoxycinnamate, Cetyl PEG/PPG-10/1 Dimethicone, Mica (CI 77019), Niacinamide, Dicaprylyl Carbonate, Lauryl PEG-9 Polydimethylsiloxyethyl Dimethicone, Bis-Ethylhexyloxyphenol Methoxyphenyl Triazine, Cyclohexasiloxane, Ceresin, Iron Oxides (CI 77491), Diisostearyl Malate, Sodium Chloride, Polyester-1, Silica, Silica Dimethyl Silylate, Disteardimonium Hectorite, Sorbitan Sesquioleate, Synthetic Wax, Sorbitan Olivate, Iron Oxides (CI 77499), Vegetable Oil, Chlorphenesin, Dipropylene Glycol, Citrus Aurantium Bergamia (Bergamot) Fruit Oil, Citrus Aurantium Dulcis (Orange) Oil, 1,2-Hexanediol, Propylene Carbonate, Hydroxyacetophenone, Dimethicone, Cananga Odorata Flower Oil, Adenosine, Disodium EDTA, Natto Gum, Saussurea Involucrata Extract, Bambusa Vulgaris Leaf/Stem Extract, Vaccinium Angustifolium (Blueberry) Fruit Extract, Cocos Nucifera (Coconut) Oil, Tocopheryl Acetate, Hydrolyzed Hyaluronic Acid, Tocopherol